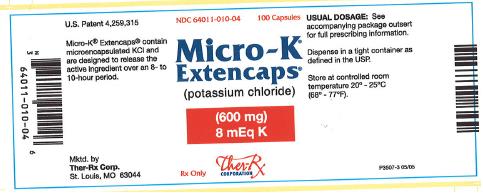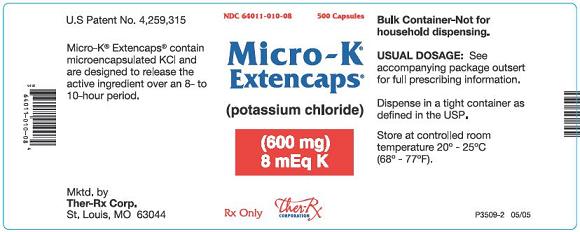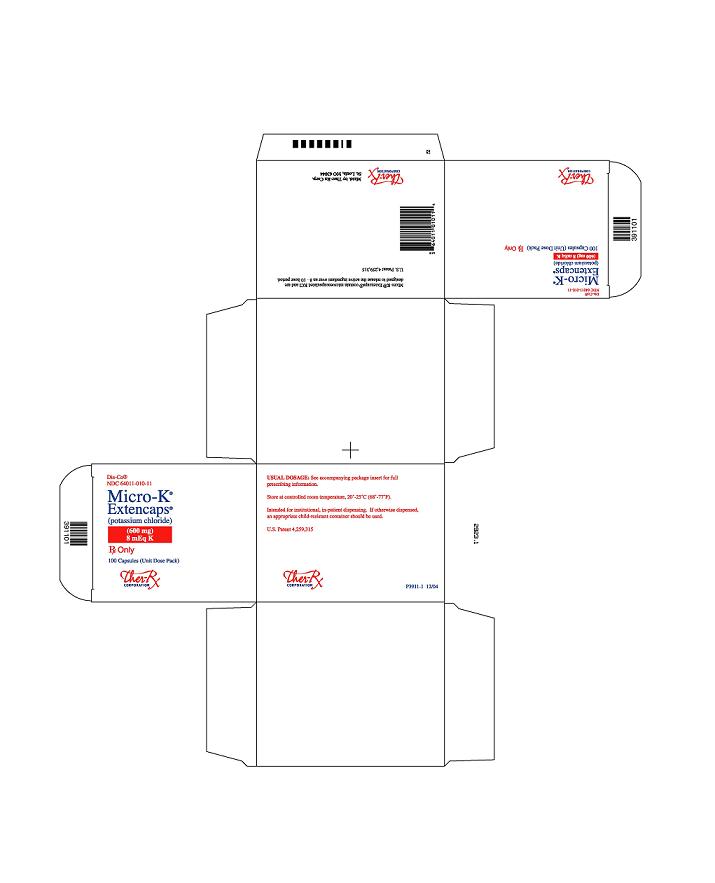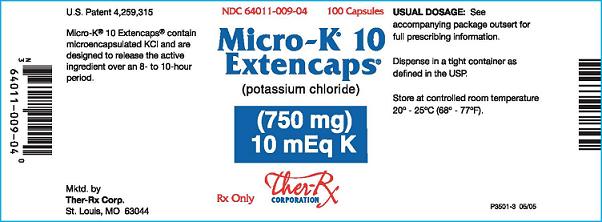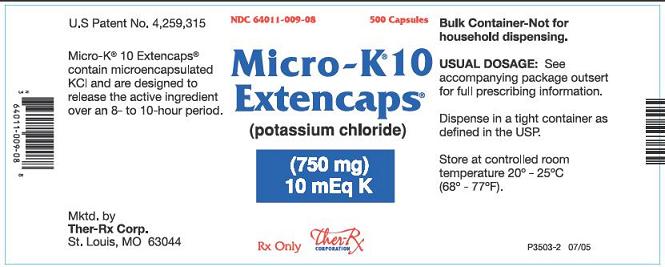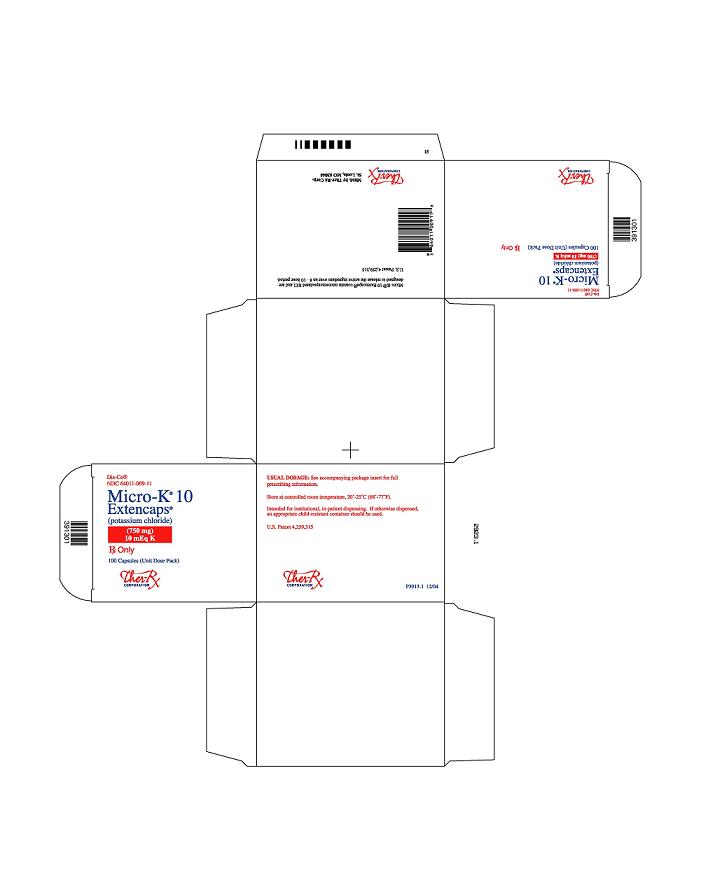 DRUG LABEL: Micro-K Extencaps
NDC: 64011-010 | Form: CAPSULE, EXTENDED RELEASE
Manufacturer: Ther-Rx Corporation
Category: prescription | Type: HUMAN PRESCRIPTION DRUG LABEL
Date: 20091221

ACTIVE INGREDIENTS: POTASSIUM CHLORIDE 600 mg/1 1
INACTIVE INGREDIENTS: ETHYLCELLULOSE (100 CPS); FD&C BLUE NO. 2; FD&C YELLOW NO. 6; GELATIN; MAGNESIUM STEARATE; SODIUM LAURYL SULFATE; TITANIUM DIOXIDE; FD&C RED NO. 40

Micro-K® Extencaps®
Micro-K® 10 Extencaps®
(Potassium Chloride Extended-Release Capsules, USP)

U.S. Patent No. 4,259,315
Rx Only
P3511-4 06/05

DESCRIPTION

Micro-K® Extencaps® Capsules and Micro-K® 10 Extencaps® Capsules are oral dosage forms of microencapsulated potassium chloride containing 600 and 750 mg, respectively, of potassium chloride, USP, equivalent to 8 and 10 mEq of potassium, respectively.

Dispersibility of potassium chloride (KCI) is accomplished by microencapsulation and a dispersing agent. The resultant flow characteristics of the KCI microcapsules and the controlled release of K^+ ions by the microcapsular membrane are intended to avoid the possibility that excessive amounts of KCI can be localized at any point on the mucosa of the gastrointestinal tract.

Each crystal of KCI is microencapsulated by a patented process with an insoluble polymeric coating which functions as a semi-permeable membrane; it allows for the controlled release of potassium and chloride ions over an eight-to ten-hour period. Fluids pass through the membrane and gradually dissolve the potassium chloride within the microcapsules. The resulting potassium chloride solution slowly diffuses outward through the membrane. Micro-K® and Micro-K® 10 are electrolyte replenishers. The chemical name of the active ingredient is potassium chloride and the structural formula is KCI. Potassium chloride, USP, occurs as a white, granular powder or as colorless crystals. It is odorless and has a saline taste. Its solutions are neutral to litmus. It is freely soluble in water and insoluble in alcohol.

The inactive ingredients are edible ink, ethylcellulose, FD&C Blue No. 2 aluminum lake, FD&C Yellow No. 6, gelatin, magnesium stearate, sodium lauryl sulfate, titanium dioxide. May contain FD&C Red No. 40 and Yellow No. 6 aluminum lakes.

CLINICAL PHARMACOLOGY

Potassium ion is the principal intracellular cation of most body tissues. Potassium ions participate in a number of essential physiological processes, including the maintenance of intracellular tonicity, the transmission of nerve impulses, the contraction of cardiac, skeletal, and smooth muscle, and the maintenance of normal renal function.

The intracellular concentration of potassium is approximately 150 to 160 mEq per liter. The normal adult plasma concentration is 3.5 to 5 mEq per liter. An active ion transport system maintains this gradient across the plasma membrane.

Potassium is a normal dietary constituent and under steady-state conditions the amount of potassium absorbed from the gastrointestinal tract is equal to the amount excreted in the urine. The usual dietary intake of potassium is 50 to 100 mEq per day.

Potassium depletion will occur whenever the rate of potassium loss through renal excretion and/or loss from the gastrointestinal tract exceeds the rate of potassium intake. Such depletion usually develops slowly as a consequence of therapy with diuretics, primary or secondary hyperaldosteronisms, diabetic ketoacidosis, or inadequate replacement of potassium in patients on prolonged parenteral nutrition. Depletion can develop rapidly with severe diarrhea, especially if associated with vomiting. Potassium depletion due to these causes is usually accompanied by a concomitant loss of chloride and is manifested by hypokalemia and metabolic alkalosis. Potassium depletion may produce weakness, fatigue, disturbances of cardiac rhythm (primarily ectopic beats), prominent U-waves in the electrocardiogram, and in advanced cases, flaccid paralysis and/or impaired ability to concentrate urine.

If potassium depletion associated with metabolic alkalosis cannot be managed by correcting the fundamental cause of the deficiency, e.g., where the patient requires long-term diuretic therapy, supplemental potassium in the form of high potassium food or potassium chloride may be able to restore normal potassium levels.

In rare circumstances (e.g., patients with renal tubular acidosis) potassium depletion may be associated with metabolic acidosis and hyperchloremia. In such patients potassium replacement should be accomplished with potassium salts other than the chloride, such as potassium bicarbonate, potassium citrate, potassium acetate, or potassium gluconate.

INDICATIONS AND USAGE

BECAUSE OF REPORTS OF INTESTINAL AND GASTRIC ULCERATION AND BLEEDING WITH CONTROLLED-RELEASE POTASSIUM CHLORIDE PREPARATIONS, THESE DRUGS SHOULD BE RESERVED FOR THOSE PATIENTS WHO CANNOT TOLERATE OR REFUSE TO TAKE LIQUID OR EFFERVESCENT POTASSIUM PREPARATIONS OR FOR PATIENTS IN WHOM THERE IS A PROBLEM OF COMPLIANCE WITH THESE PREPARATIONS.

1. For the treatment of patients with hypokalemia with or without metabolic alkalosis, in digitalis intoxications, and in patients with hypokalemic familial periodic paralysis. If hypokalemia is the result of diuretic therapy, consideration should be given to the use of a lower dose of diuretic, which may be sufficient without leading to hypokalemia.
2. For the prevention of hypokalemia in patients who would be at particular risk if hypokalemia were to develop e.g., digitalized patients or patients with significant cardiac arrhythmias, hepatic cirrhosis with ascites, states of aldosterone excess with normal renal function, potassium-losing nephropathy, and certain diarrheal states.

The use of potassium salts in patients receiving diuretics for uncomplicated essential hypertension is often unnecessary when such patients have a normal dietary pattern and when low doses of the diuretic are used. Serum potassium should be checked periodically, however, and if hypokalemia occurs, dietary supplementation with potassium-containing foods may be adequate to control milder cases. In more severe cases, and if dose adjustment of the diuretic is ineffective or unwarranted, supplementation with potassium salts may be indicated.

CONTRAINDICATIONS

Potassium supplements are contraindicated in patients with hyperkalemia since a further increase in serum potassium concentration in such patients can produce cardiac arrest. Hyperkalemia may complicate any of the following conditions: chronic renal failure, systemic acidosis such as diabetic acidosis, acute dehydration, extensive tissue breakdown as in severe burns, adrenal insufficiency, or the administration of a potassium-sparing diuretic (e.g., spironolactone, triamterene, amiloride) (see OVERDOSAGE).

Controlled-release formulations of potassium chloride have produced esophageal ulceration in certain cardiac patients with esophageal compression due to an enlarged left atrium. Potassium supplementation, when indicated in such patients, should be given as a liquid preparation.

All solid oral dosage forms of potassium chloride are contraindicated in any patient in whom there is structural, pathological (e.g., diabetic gastroparesis) or pharmacologic (use of anticholinergic agents or other agents with anticholineric properties at sufficient doses to exert anticholinergic effects) cause for arrest or delay in capsule passage through the gastrointestinal tract.

WARNINGS

Hyperkalemia (see OVERDOSAGE)

In patients with impaired mechanisms for excreting potassium, the administration of potassium salts can produce hyperkalemia and cardiac arrest. This occurs most commonly in patients given potassium by the intravenous route but may also occur in patients given potassium orally. Potentially fatal hyperkalemia can develop rapidly and be asymptomatic. The use of potassium salts in patients with chronic renal disease, or any other condition which impairs potassium excretion, requires particularly careful monitoring of the serum potassium concentration and appropriate dosage adjustments.

Interaction with Potassium-Sparing Diuretics

Hypokalemia should not be treated by the concomitant administration of potassium salts and a potassium-sparing diuretic (e.g., spironolactone, triamterene, or amiloride), since the simultaneous administration of these agents can produce severe hyperkalemia.

Interaction with Angiotensin Converting Enzyme Inhibitors

Angiotensin converting enzyme (ACE) inhibitors (e.g., captopril, enalapril) will produce some potassium retention by inhibiting aldosterone production. Potassium supplements should be given to patients receiving ACE inhibitors only with close monitoring.

Gastrointestinal Lesions

Solid oral dosage forms of potassium chloride can produce ulcerative and/or stenotic lesions of the gastrointestinal tract. Based on spontaneous adverse reaction reports, enteric-coated preparations of potassium chloride are associated with an increased frequency of small bowel lesions (40 - 50 per 100,000 patient years) compared to sustained-release wax matrix formulations (less than one per 100,000 patient years). Because of the lack of extensive marketing experience with microencapsulated products, a comparison between such products and wax matrix or enteric-coated products is not available. Micro-K® Extencaps® and Micro-K® 10 Extencaps® are microencapsulated capsules formulated to provide a controlled rate of release of microencapsulated potassium chloride and thus to minimize the possibility of high local concentration of potassium near the gastrointestinal wall.

Prospective trials have been conducted in normal human volunteers in which the upper gastrointestinal tract was evaluated by endoscopic inspection before and after one week of solid oral potassium chloride therapy. The ability of this model to predict events occurring in usual clinical practice is unknown. Trials which approximated usual clinical practice did not reveal any clear differences between the wax matrix and microencapsulated dosage forms. In contrast, there was a higher incidence of gastric and duodenal lesions in subjects receiving a high dose of a wax matrix controlled-release formulation under conditions which did not resemble usual or recommended clinical practice (i.e., 96 mEq per day in divided doses of potassium chloride administered to fasted patients, in the presence of an anticholinergic drug to delay gastric emptying). The upper gastrointestinal lesions observed by endoscopy were asymptomatic and were not accompanied by evidence of bleeding (hemoccult testing). The relevance of these findings to the usual conditions (i.e., non-fasting, no anticholinergic agent, smaller doses) under which controlled-release potassium chloride products are used is uncertain; epidemiologic studies have not identified an elevated risk, compared to microencapsulated products, for upper gastrointestinal lesions in patients receiving wax matrix formulations. Micro-K® Extencaps® and Micro-K® 10 Extencaps® should be discontinued immediately and the possibility of ulceration, obstruction or perforation considered if severe vomiting, abdominal pain, distention, or gastrointestinal bleeding occur.

Metabolic Acidosis

Hypokalemia in patients with metabolic acidosis should be treated with an alkalinizing potassium salt such as potassium bicarbonate, potassium citrate, potassium acetate, or potassium gluconate.

PRECAUTIONS:

General

The diagnosis of potassium depletion is ordinarily made by demonstrating hypokalemia in a patient with a clinical history suggesting some cause for potassium depletion. In interpreting the serum potassium level, the physician should bear in mind that acute alkalosis per se can produce hypokalemia in the absence of a deficit in total body potassium, while acute acidosis per se can increase the serum potassium concentration into the normal range even in the presence of a reduced total body potassium. The treatment of potassium depletion, particularly in the presence of cardiac disease, renal disease, or acidosis, requires careful attention to acid-base balance and appropriate monitoring of serum electrolytes, the electrocardiogram, and the clinical status of the patient.

Information for Patients

Physicians should consider reminding the patient of the following: To take each dose with meals and with a full glass of water or other suitable liquid. To take each dose without crushing, chewing, or sucking the capsules. To take this medicine following the frequency and amount prescribed by the physician. This is especially important if the patient is also taking diuretics and/or digitalis preparations. To check with the physician if there is trouble swallowing capsules or if the capsules seem to stick in the throat.

To check with the physician at once if tarry stools or other evidence of gastrointestinal bleeding is noticed.

Laboratory Tests

Regular serum potassium determinations are recommended, especially in patients with renal insufficiency or diabetic nephropathy. When blood is drawn for analysis of plasma potassium it is important to recognize that artifactual elevations can occur after improper venipuncture technique or as a result of in vitro hemolysis of the sample.

Drug Interactions

Potassium-sparing diuretics, angiotensin converting enzyme inhibitors (see WARNINGS).

Carcinogenesis, Mutagenesis, Impairment of Fertility

Carcinogenicity, mutagenicity and fertility studies in animals have not been performed. Potassium is a normal dietary constituent.

Pregnancy

TERATOGENIC EFFECTS

Teratogenic Effects: Category C Animal reproduction studies have not been conducted with Micro-K®. It is unlikely that potassium supplementation that does not lead to hyperkalemia would have an adverse effect on the fetus or would affect reproductive capacity.

Nursing Mothers

The normal potassium ion content of human milk is about 13 mEq per liter. Since oral potassium becomes part of the body potassium pool, so long as body potassium is not excessive, the contribution of potassium chloride supplementation should have little or no effect on the level in human milk.

Pediatric Use

Safety and effectiveness in pediatric patients have not been established.

Geriatric Use

Clinical studies of potassium chloride extended-release capsules did not include sufficient numbers of subjects aged 65 and over to determine whether they respond differently from younger subjects. Other reported clinical experience has not identified differences in responses between the elderly and younger patients. In general, dose selection for an elderly patient should be cautious, usually starting at the low end of the dosing range, reflecting the greater frequency of decreased hepatic, renal, or cardiac function, and of concomitant disease or other drug therapy.

This drug is known to be substantially excreted by the kidney, and the risk of toxic reactions to this drug may be greater in patients with impaired renal function. Because elderly patients are more likely to have decreased renal function, care should be taken in dose selection, and it may be useful to monitor renal function.

ADVERSE REACTIONS

One of the most severe adverse effects is hyperkalemia (see CONTRAINDICATIONS, WARNINGS, and OVERDOSAGE). Gastrointestinal bleeding and ulceration have been reported in patients treated with Micro-K® Extencaps® (see CONTRAINDICATIONS and WARNINGS). In addition to gastrointestinal bleeding and ulceration, perforation and obstruction have been reported in patients treated with other solid KCI dosage forms, and may occur with Micro-K® Extencaps®.

The most common adverse reactions to the oral potassium salts are nausea, vomiting, flatulence, abdominal discomfort, and diarrhea. These symptoms are due to irritation of the gastrointestinal tract and are best managed by taking the dose with meals, or reducing the amount taken at one time. Skin rash has been reported rarely with potassium preparations.

OVERDOSAGE

The administration of oral potassium salts to persons with normal excretory mechanisms for potassium rarely causes serious hyperkalemia. However, if excretory mechanisms are impaired or if potassium is administered too rapidly intravenously, potentially fatal hyperkalemia can result (see CONTRAINDICATIONS and WARNINGS). It is important to recognize that hyperkalemia is usually asymptomatic and may be manifested only by an increased serum potassium concentration (6.5 - 8.0 mEq/L) and characteristic electrocardiographic changes (peaking of T-waves, loss of P-waves, depression of ST segment, and prolongation of the QT interval). Late manifestations include muscle paralysis and cardiovascular collapse from cardiac arrest (9 - 12 mEq/L).

Treatment measures for hyperkalemia include the following: (1) elimination of foods and medications containing potassium and of any agents with potassium-sparing properties; (2) intravenous administration of 300 to 500 mL/hr of 10% dextrose solution containing 10 to 20 units of crystalline insulin per 1,000 mL; (3) correction of acidosis, if present, with intravenous sodium bicarbonate; (4) use of exchange resins, hemodialysis, or peritoneal dialysis. In treating hyperkalemia, it should be recalled that in patients who have been stabilized on digitalis, too rapid a lowering of the serum potassium concentration can produce digitalis toxicity.

The extended release feature means that absorption and toxic effects may be delayed for hours. Consider standard measures to remove any unabsorbed drug.

DOSAGE AND ADMINISTRATION

The usual dietary intake of potassium by the average adult is 50 to 100 mEq per day. Potassium depletion sufficient to cause hypokalemia usually requires the loss of 200 mEq or more of potassium from the total body store.

Dosage must be adjusted to the individual needs of each patient. The dose for the prevention of hypokalemia is typically in the range of 20 mEq per day. Doses of 40 to 100 mEq per day or more are used for the treatment of potassium depletion. Dosage should be divided if more than 20 mEq per day is given such that no more than 20 mEq is given in a single dose. Because of the potential for gastric irritation (see WARNINGS), Micro-K® Extencaps® should be taken with meals and with a full glass of water or other liquid.

Patients who have difficulty swallowing capsules may sprinkle the contents of the capsule onto a spoonful of soft food. The soft food, such as applesauce or pudding, should be swallowed immediately without chewing and followed with a glass of cool water or juice to ensure complete swallowing of the microcapsules. The food used should not be hot and should be soft enough to be swallowed without chewing. Any microcapsule/food mixture should be used immediately and not stored for future use.

HOW SUPPLIED

Micro-K® Extencaps containing 600 mg of microencapsulated potassium chloride (equivalent to 8 mEq K), are pale orange capsules, imprinted "Micro-K" on the cap and "Ther-Rx 010" on the body, packaged as follows:
NDC 64011-010-04 bottle of 100 capsules
NDC 64011-010-08 bottle of 500 capsules
NDC 64011-010-11 Dis-Co® unit dose packages of 100 capsules

Micro-K® 10 Extencaps® containing 750 mg of microencapsulated potassium chloride (equivalent to 10 mEq K), are pale orange and opaque white capsules, imprinted "Micro-K 10" on the cap and "Ther-Rx 009" on the body, packaged as follows:
NDC 64011-009-04 bottle of 100 capsules
NDC 64011-009-08 bottle of 500 capsules
NDC 64011-009-11 Dis-Co® unit dose packages of 100 capsules

Store at controlled room temperature 20°-25°C (68°-77°F).

Dispense in tight container.

Mktd. by Ther-Rx Corp. St. Louis, MO 63044

06/05
P3511-4

PACKAGE LABEL

NDC 64011-010-04 100 Capsules

Micro-K
Extencaps
(potassium chloride)

(600 mg)
8 mEq K

Rx Only Ther-Rx Corporation

NDC 64011-010-08 500 Capsules

Micro-K
Extencaps
(potassium chloride)

(600 mg)
8 mEq K

Rx Only Ther-Rx Corporation

Dis-Co
NDC 64011-010-11

Micro-K
Extencaps
(potassium chloride)

(600 mg)
8 mEq K

Rx Only
100 Capsules (Unit Dose Pack)
Ther-Rx Corporation

NDC 64011-009-04 100 Capsules

Micro-K 10
Extencaps
(potassium chloride)

(750 mg)
10 mEq K

Rx Only Ther-Rx Corporation

NDC 64011-009-08 500 Capsules

Micro-K 10
Extencaps
(potassium chloride)

(750 mg)
10 mEq K

Rx Only Ther-Rx Corporation

Dis-Co
NDC 64011-009-11

Micro-K
Extencaps
(potassium chloride)

(750 mg)
10 mEq K

Rx Only
100 Capsules (Unit Dose Pack)
Ther-Rx Corporation